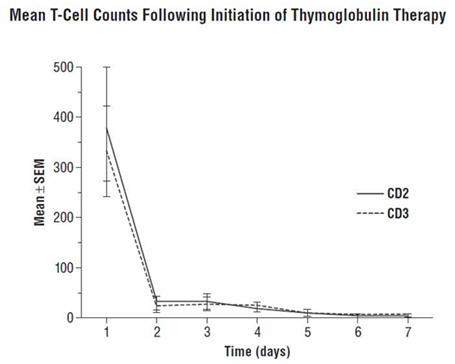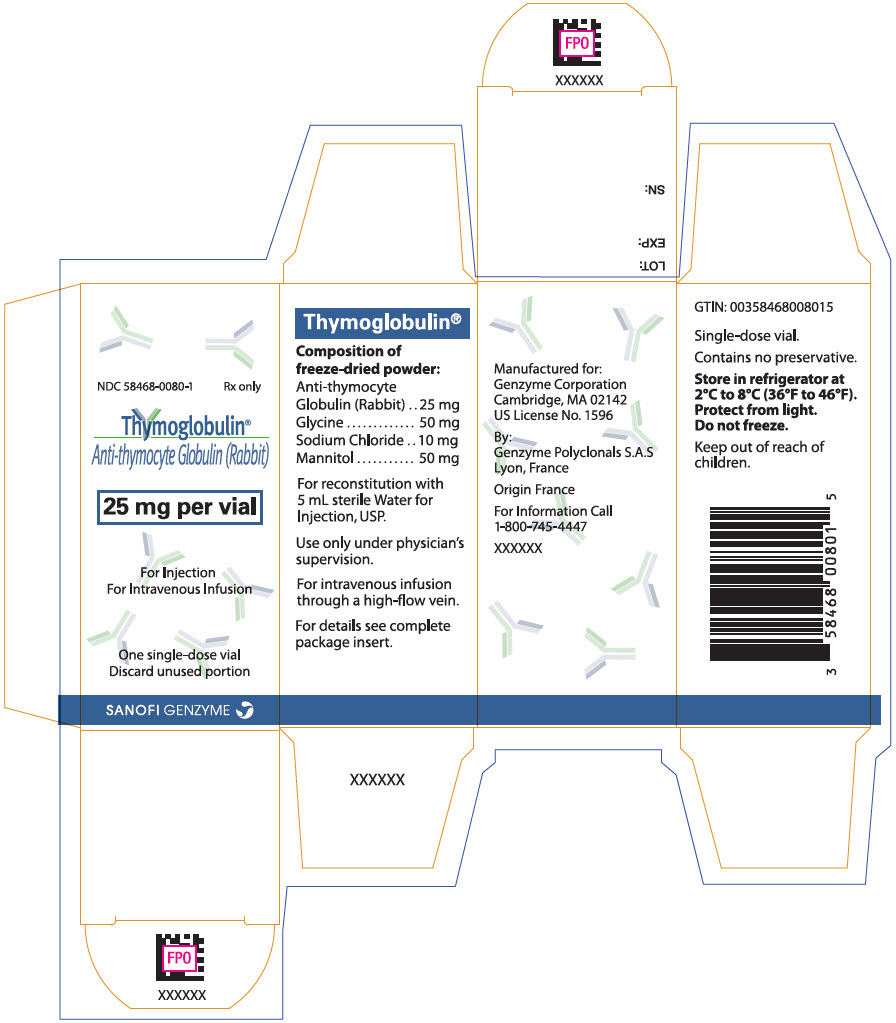 DRUG LABEL: Thymoglobulin
NDC: 58468-0080 | Form: INJECTION, POWDER, LYOPHILIZED, FOR SOLUTION
Manufacturer: Genzyme Corporation
Category: prescription | Type: HUMAN PRESCRIPTION DRUG LABEL
Date: 20260131

ACTIVE INGREDIENTS: LAPINE T-LYMPHOCYTE IMMUNE GLOBULIN 5 mg/1 mL
INACTIVE INGREDIENTS: GLYCINE; SODIUM CHLORIDE; MANNITOL

HIGHLIGHTS OF PRESCRIBING INFORMATION

These highlights do not include all the information needed to use THYMOGLOBULIN® safely and effectively. See full prescribing information for THYMOGLOBULIN.
THYMOGLOBULIN (anti-thymocyte globulin [rabbit]) for injection, for intravenous use
Initial U.S. Approval: 1998

1 INDICATIONS AND USAGE

- THYMOGLOBULIN is an immunoglobulin G indicated for the prophylaxis and treatment of acute rejection in adult and pediatric patients receiving a kidney transplant in conjunction with concomitant immunosuppression. (1)

2 DOSAGE AND ADMINISTRATION

- The first dose should be infused over at least 6 hours; doses on subsequent days should be infused over at least 4 hours. (2.2)
- Premedication with corticosteroids, acetaminophen, and/or an antihistamine prior to each infusion is recommended. (2.2)
- The THYMOGLOBULIN dose should be reduced by one-half if the white blood cell (WBC) count is between 2,000 and 3,000 cells/mm^3 or if the platelet count is between 50,000 and 75,000 cells/mm^3. Stopping THYMOGLOBULIN treatment should be considered if the WBC count falls below 2,000 cells/mm^3 or if the platelet count falls below 50,000 cells/mm^3. (2.3)

Indication | Dose
Prophylaxis of acute rejection | 1.5 mg/kg of body weight administered daily for 4 to 7 days
Treatment of acute rejection | 1.5 mg/kg of body weight administered daily for 7 to 14 days

For complete dosing instructions, see full prescribing information. (2)

3 DOSAGE FORMS AND STRENGTHS

- Single-dose 10 mL vial containing 25 mg of anti-thymocyte globulin (rabbit) lyophilized, sterile powder. (3)

4 CONTRAINDICATIONS

Allergy or anaphylactic reaction to rabbit proteins or to any product excipients, or active acute or chronic infections which contraindicate any additional immunosuppression (4)

5 WARNINGS AND PRECAUTIONS

- THYMOGLOBULIN should only be used by physicians experienced in immunosuppressant therapy in transplantation. (5.1)
- Hypersensitivity and infusion-related reactions: THYMOGLOBULIN infusion could result in an anaphylactic reaction. Close compliance with the recommended infusion time may reduce the incidence and severity of infusion-related reactions. (5.2)
- Cytopenias including anemia, neutropenia, and thrombocytopenia have occurred with THYMOGLOBULIN administration (6) and require monitoring of blood counts. Adjust dose accordingly to reverse cytopenias. (5.3)
- Infection: Infections and reactivation of infections have been reported. Monitor patients and administer anti-infective prophylaxis. (5.4)
- Malignancy: Incidence of malignancies may increase. (5.5)
- Immunization with attenuated live vaccines is not recommended for patients who have recently received THYMOGLOBULIN. (5.6)
- THYMOGLOBULIN may interfere with rabbit antibody–based immunoassays and with cross-match or panel-reactive antibody cytotoxicity assays. (5.7)

6 ADVERSE REACTIONS

The most common adverse reactions and laboratory abnormalities (incidence >5% higher than comparator) are urinary tract infection, abdominal pain, hypertension, nausea, shortness of breath, fever, headache, anxiety, chills, increased potassium levels in the blood, low counts of platelets and white blood cells. (6)

To report SUSPECTED ADVERSE REACTIONS, contact Genzyme Corporation at 1-800-633-1610 or FDA at 1-800-FDA-1088 or www.fda.gov/medwatch.

FULL PRESCRIBING INFORMATION

1 INDICATIONS AND USAGE

THYMOGLOBULIN is indicated for the prophylaxis and treatment of acute rejection in adult and pediatric patients receiving a kidney transplant in conjunction with concomitant immunosuppression.

2 DOSAGE AND ADMINISTRATION

2.1 Dosing Information

For intravenous use only

Prophylaxis of Acute Rejection

The recommended dosage of THYMOGLOBULIN for prophylaxis of acute rejection in patients receiving a kidney transplant is 1.5 mg/kg of body weight administered daily with the first dose initiated prior to reperfusion of the donor kidney. The usual duration of administration is 4 to 7 days.

Treatment of Acute Rejection

The recommended dosage of THYMOGLOBULIN for treatment of acute rejection in patients receiving a kidney transplant is 1.5 mg/kg of body weight administered daily for 7 to 14 days.

Dosing for THYMOGLOBULIN is different from dosing for other anti-thymocyte globulin (ATG) products, because protein composition and concentrations vary depending on the source of ATG. The prescribing physician must ensure that the dose prescribed is appropriate for the ATG product being administered.

2.2 Recommended Dosing Regimen

Administer the first dose of THYMOGLOBULIN over a minimum of 6 hours; administer doses on subsequent days over at least 4 hours [see Warnings and Precautions (5.2)].

Premedicate with corticosteroids, acetaminophen, and/or an antihistamine 1 hour prior to each infusion of THYMOGLOBULIN to reduce the incidence and intensity of infusion-related reactions [see Warnings and Precautions (5.2) and Adverse Reactions (6.1)].

2.3 Dose Modifications

Monitor patients for adverse reactions during and after infusion. Monitor total white blood cell and platelet counts during and after THYMOGLOBULIN therapy.

Reduce the THYMOGLOBULIN dose by one-half if the white blood cell (WBC) count is between 2,000 and 3,000 cells/mm^3 or if the platelet count is between 50,000 and 75,000 cells/mm^3. Consider stopping THYMOGLOBULIN treatment if the WBC count falls below 2,000 cells/mm^3 or if the platelet count falls below 50,000 cells/mm^3.

2.4 Recommended Concomitant Medication

THYMOGLOBULIN is used with concomitant immunosuppressants.

Administer prophylactic antifungal and antibacterial therapy if clinically indicated [see Warnings and Precautions (5.4)].

Antiviral prophylactic therapy is recommended for patients who are seropositive for cytomegalovirus (CMV) at the time of transplant and for CMV-seronegative patients scheduled to receive a kidney from a CMV-seropositive donor [see Warnings and Precautions (5.4)].

2.5 Instructions for Dilution and Administration

Reconstitution

After calculating the number of vials needed, using aseptic technique, reconstitute each vial of THYMOGLOBULIN with 5 mL of Sterile Water for Injection, USP (SWFI).

1. Allow THYMOGLOBULIN vials to reach room temperature before reconstituting the lyophilized product.
2. Aseptically remove caps to expose rubber stoppers.
3. Clean stoppers with germicidal or alcohol swab.
4. Aseptically reconstitute each vial of THYMOGLOBULIN lyophilized powder with the 5 mL of SWFI.
5. Rotate vial gently until powder is completely dissolved. Each reconstituted vial contains 25 mg or 5 mg/mL of THYMOGLOBULIN.
6. Inspect solution for particulate matter after reconstitution. Should some particulate matter remain, continue to gently rotate the vial until no particulate matter is visible. If particulate matter persists, discard this vial.

Dilution

1. Transfer the contents of the calculated number of THYMOGLOBULIN vials into the bag of infusion solution (saline or dextrose). Recommended volume: per one vial of THYMOGLOBULIN use 50 mL of infusion solution (total volume usually between 50 to 500 mL). Discard unused portion.
2. Mix the solution by inverting the bag gently only once or twice.

Infusion

Administer THYMOGLOBULIN under strict medical supervision in a hospital setting, and carefully monitor patients during the infusion.

THYMOGLOBULIN is less likely to produce side effects when administered at the recommended flow rate [see Warnings and Precautions (5.2)].

1. Follow the manufacturer's instructions for the infusion administration set. Infuse through a 0.22 micrometer filter into a high-flow vein.
2. Set the flow rate to deliver the dose over a minimum of 6 hours for the first dose and over at least 4 hours for subsequent doses.

3 DOSAGE FORMS AND STRENGTHS

THYMOGLOBULIN for injection: 25 mg anti-thymocyte globulin (rabbit) as a sterile lyophilized powder, in single-dose 10 mL vials for reconstitution.

4 CONTRAINDICATIONS

THYMOGLOBULIN is contraindicated in patients with history of allergy or anaphylactic reaction to rabbit proteins or to any product excipients, or who have active acute or chronic infections that contraindicate any additional immunosuppression [see Warnings and Precautions (5.2, 5.4) and Adverse Reactions (6.2)].

5 WARNINGS AND PRECAUTIONS

5.1 Management of Immunosuppression

To prevent over-immunosuppression, physicians may wish to decrease the dose of the maintenance immunosuppression regimen during the period of THYMOGLOBULIN use.

5.2 Hypersensitivity and Infusion-Related Reactions

Severe hypersensitivity and infusion-related reactions, including fatal anaphylaxis and severe cytokine release syndrome (CRS), have been reported with the use of THYMOGLOBULIN [see Adverse Reactions (6)]. Severe acute CRS can cause serious cardiorespiratory events and/or death. Close compliance with the recommended dosage and infusion time may reduce the incidence and severity of infusion-related reactions. Slowing the infusion rate may minimize the risk of infusion-related reactions.

If a hypersensitivity or infusion-related reaction occurs, terminate the infusion immediately and provide supportive treatment according to clinical practice.

5.3 Cytopenias

Cytopenias including anemia, neutropenia, and thrombocytopenia have occurred with THYMOGLOBULIN administration [see Adverse Reactions (6)]. Monitors blood counts after THYMOGLOBULIN administration. Adjust dose accordingly to reverse cytopenias [see Dosage and Administration (2.3)].

5.4 Infection

THYMOGLOBULIN is routinely used in combination with other immunosuppressive agents. Infections (bacterial, fungal, viral and protozoal), reactivation of infection (particularly cytomegalovirus [CMV]) and sepsis have been reported after THYMOGLOBULIN administration in combination with multiple immunosuppressive agents [see Adverse Reactions (6)]. These infections can be fatal.

Monitor patients carefully and administer appropriate anti-infective treatment when indicated [see Dosage and Administration (2.4)].

5.5 Malignancy

Malignancies with fatal outcomes have been reported in patients treated with THYMOGLOBULIN [see Adverse Reactions (6)]. Use of immunosuppressive agents, including THYMOGLOBULIN, may increase the risk of malignancies, including lymphoma or lymphoproliferative disorders.

5.6 Immunizations

The safety of immunization with attenuated live vaccines following THYMOGLOBULIN therapy has not been studied; therefore, immunization with attenuated live vaccines is not recommended for patients who have recently received THYMOGLOBULIN.

5.7 Laboratory Tests

THYMOGLOBULIN may interfere with rabbit antibody–based immunoassays and with cross-match or panel-reactive antibody cytotoxicity assays. THYMOGLOBULIN has not been shown to interfere with any routine clinical laboratory tests that do not use immunoglobulins.

6 ADVERSE REACTIONS

6.1 Clinical Trials Experience

Because clinical trials are conducted under widely varying conditions, adverse reaction rates observed in the clinical trials of a drug cannot be directly compared to rates in the clinical trials of another drug and may not reflect the rates observed in practice.

The most common adverse reactions and laboratory abnormalities (incidence >5% higher than comparator) are urinary tract infection, abdominal pain, hypertension, nausea, shortness of breath, fever, headache, anxiety, chills, increased potassium levels in the blood, and low counts of platelets and white blood cells.

Prophylaxis of Acute Rejection

The safety of THYMOGLOBULIN compared to Active Comparator for the prophylaxis of acute rejection in patients receiving a kidney transplant were evaluated in a randomized, open-label, international, multicenter trial in patients receiving solitary kidneys from deceased donors (n=278; Study 1).

Table 1: Adverse Reactions [Adverse reactions are treatment emergent adverse events (TEAE) reported as related to the study agent in at least 1 patient.] and Laboratory Abnormalities Reported More Frequently (incidence [Number (percentage) is shown regardless of causal relationship.] >5%) Following THYMOGLOBULIN versus Active Comparator [basiliximab]
Adverse Reaction [n (%)] | THYMOGLOBULIN (N=141) | Active Comparator (N=137)
Urinary tract infection | 55 (39%) | 36 (26%)
Pyrexia | 39 (28%) | 25 (18%)
Headache | 26 (18%) | 17 (12%)
Hyperlipidemia | 21 (15%) | 9 (7%)
Anxiety | 20 (14%) | 12 (9%)
Chills | 13 (9%) | 5 (4%)
Laboratory Abnormalities [Hyperkalemia: blood potassium ≥5.5 mmol/L; Leukopenia: WBC <3000 cells/mm^3. Thrombocytopenia: platelet count <75,000 cells/mm^3.]
Hyperkalemia | 81 (57%) | 70 (51%)
Leukopenia | 89 (63%) | 20 (15%)
Thrombocytopenia | 23 (16%) | 7 (5%)

Malignancies

Six patients in the THYMOGLOBULIN group developed malignancies (Epstein-Barr virus-induced lymphoma of the cavum, Epstein-Barr virus-positive large B-cell lung lymphoma, Epstein-Barr virus-induced lymphoma of the brain, squamous cell carcinoma, renal cancer, and recurrent basal cell carcinoma). In the Active Comparator group, 1 patient developed renal cancer.

Infections

Infections occurred in 76% of THYMOGLOBULIN-treated patients (severe in 23%), and in 63% of Active Comparator-treated patients (severe in 15%).

Infections occurring in ≥5% of the patients in either treatment group during the 12-month follow-up are summarized in Table 2. Urinary tract infection was the most frequent type of infection, and was reported as severe in 9% of THYMOGLOBULIN-treated patients and in 2% of Active Comparator-treated patients. CMV infections were reported more frequently in the Active Comparator group, with an incidence of 6% (severe in 1%) in THYMOGLOBULIN-treated patients and of 18% (severe in 7%) in Active Comparator-treated patients. Patients who were CMV-positive at the time of transplant, as well as CMV-negative recipients of transplants from CMV-positive donors, were required to receive antiviral prophylaxis for 3 months after transplant.

Table 2: Infections Reported in ≥5% of Study Patients
Infection | THYMOGLOBULIN (N=141) |  | Active Comparator [basiliximab] (N=137)
Infection | All | Severe/Unknown | All | Severe/Unknown
Urinary tract infections [Urinary tract infection group includes: Urinary tract infections, Urinary tract infection fungal, Urinary tract infection bacterial, Bacterial pyelonephritis, Urosepsis.] | 59 (42%) | 12 (9%) | 39 (29%) | 3 (2%)
Sepsis [Sepsis group includes: Sepsis, Escherichia sepsis, Staphylococcal bacteremia.] | 9 (6%) | 5 (4%) | 1 (1%) | 1 (1%)
Lower respiratory tract and lung infections [Lower respiratory tract and lung infections group includes: Lower respiratory tract and lung infections, and Pneumonia pseudomonal.] | 18 (13%) | 2 (1%) | 16 (12%) | 4 (3%)
Upper respiratory tract infection | 15 (11%) | 0 | 15 (11%) | 1 (1%)
Nasopharyngitis | 7 (5%) | 0 | 9 (7%) | 0
Cytomegaloviral infections [The collective term "cytomegaloviral infections" includes CMV duodenitis, CMV gastritis, CMV hepatitis, CMV infection, and CMV viremia.] | 8 (6%) | 2 (1%) | 21 (18%) | 7 (7%)
Herpes zoster | 7 (5%) | 0 | 2 (2%) | 1 (1%)
Oral candidiasis | 8 (6%) | 0 | 11 (8%) | 0

Adverse Drug Reactions Occurring within 24 Hours and Infusion-Related Reactions

Adverse reactions occurring during or within 24 hours of infusion in >5% of patients in the THYMOGLOBULIN group are summarized in Table 3.

Table 3: Adverse Drug Reactions [Adverse reactions that occurred during or within 24 hours of an infusion, and where the incidence was higher in the THYMOGLOBULIN group.] Occurring within 24 Hours of Infusion and with >5% Incidence in Patients who Received THYMOGLOBULIN
Primary System Organ Class n (%) | THYMOGLOBULIN (N=141) | Active Comparator [basiliximab] (N=137)
Constipation | 47 (33%) | 23 (17%)
Anemia | 35 (25%) | 19 (14%)
Hyperkalemia | 33 (23%) | 18 (13%)
Hypertension | 25 (18%) | 19 (14%)
Leukopenia and White blood cell count decreased | 29 (21%) | 0
Pyrexia | 18 (13%) | 3 (2%)
Vomiting | 17 (12%) | 14 (10%)
Thrombocytopenia | 13 (9%) | 1 (1%)
Abdominal pain | 11 (8%) | 6 (4%)
Anxiety | 10 (7%) | 2 (2%)
Hyperphosphatemia | 10 (7%) | 2 (2%)
Tachycardia | 10 (7%) | 5 (4%)
Acidosis | 9 (6%) | 8 (6%)
Diarrhea | 9 (6%) | 1 (1%)
Hypokalemia | 9 (6%) | 4 (3%)

Infusion-related reactions

Adverse reactions that occurred within 24 hours after the completion of the THYMOGLOBULIN administration and are considered as possible infusion related reactions (IARs) include the following: anxiety, confusional state, agitation, restlessness, headache, lethargy, dizziness, decreased sensitivity, fast heart rate, myocardial infarction, elevated blood pressure, decreased blood pressure, cough, throat irritation, reduced oxygen supply to tissues, shortness of breath, pulmonary edema, pain in mouth and throat, diarrhea, upper abdominal pain, abdominal tenderness, abdominal discomfort, nausea, pruritus, rash, joint pain, fever, chills, lack of energy, localized edema, malaise, and chest pain.

Serum sickness was reported in 6 of 405 patients enrolled across completed studies where patients had been treated with THYMOGLOBULIN for the prophylaxis of acute rejection in patients receiving a kidney transplant. Anaphylactic shock was reported in 2 of 405 patients enrolled across completed studies.

Treatment of acute rejection

In the US Phase 3 randomized controlled clinical trial (n=163; Study 3) comparing the efficacy and safety of THYMOGLOBULIN and Active Comparator in the treatment of acute rejection in kidney transplant patients, adverse reactions occurring at least 5% more frequently in the THYMOGLOBULIN group than in the Active Comparator group are shown in Table 4. Malignancies were reported in 3 patients who received THYMOGLOBULIN and in 3 patients who received Active Comparator during the one-year follow-up period. These included two cases of post-transplant lymphoproliferative disease (PTLD) in the THYMOGLOBULIN group and two cases of PTLD in the Active Comparator group.

Table 4: Adverse Reactions [Treatment-emergent adverse events/reactions (TEAE) are summarized.] Reported More Frequently (incidence ≥5%) Following THYMOGLOBULIN versus Active Comparator [Anti-thymocyte globulin equine (ATG-E)]
Frequently Reported Events | THYMOGLOBULIN n=82 | Active Comparator n=81
Chills | 47 (57%) | 35 (43%)
Leukopenia | 47 (57%) | 24 (30%)
Headache | 33 (40%) | 28 (35%)
Abdominal pain | 31 (38%) | 22 (27%)
Hypertension | 30 (37%) | 23 (28%)
Nausea | 30 (37%) | 23 (28%)
Dyspnea | 23 (28%) | 16 (20%)
Hyperkalemia | 22 (27%) | 15 (19%)
Myalgia | 16 (20%) | 10 (12%)
Insomnia | 16 (20%) | 10 (12%)
Hypotension | 13 (16%) | 6 (7%)
Rash | 11 (13%) | 6 (7%)
Sweating | 11 (13%) | 4 (5%)
Malaise | 11 (13%) | 3 (4%)
Acne | 10 (12%) | 4 (5%)
Overdose | 5 (6%) | 0

Treatment-emergent thrombocytopenia was reported in 30 (37%) of patients following THYMOGLOBULIN infusion and in 36 (44%) of patients following Active Comparator infusion.

Infections occurring more frequently in the THYMOGLOBULIN group during the 3-month follow-up are summarized in Table 5. No significant differences were seen between the THYMOGLOBULIN and Active Comparator groups for all types of infections. The incidence of CMV infection was the same in both groups. Viral prophylaxis was by the center's discretion during antibody treatment, but all centers used ganciclovir infusion during treatment.

Table 5: Infections
 | THYMOGLOBULIN n=82 |  |  | Active Comparator [ATG-E] n=81
Body System | No. of Patients | (%) | Total Reports | No. of Patients | (%) | Total Reports
Body as a Whole | 30 | (37) | 36 | 22 | (27) | 29
Infection | 25 | (31) | 26 | 19 | (24) | 21
Other | 14 | (17) | 15 | 11 | (14) | 12
CMV | 11 | (13) | 11 | 9 | (11) | 9
Sepsis | 10 | (12) | 10 | 7 | (10) | 7
Digestive | 5 | (6) | 5 | 3 | (4) | 3
Gastrointestinal moniliasis | 4 | (5) | 4 | 1 | (1) | 1
Gastritis | 1 | (1) | 1 | 0 | (0) | 0
Skin | 4 | (5) | 4 | 0 | (0) | 0
Herpes simplex | 4 | (5) | 4 | 0 | (0) | 0

Adverse reactions occurring during or within 24 hours of infusion in at least 5% of patients in the THYMOGLOBULIN group are listed in Table 6.

Table 6: Adverse Reactions* Occurring within 24 Hours of Infusion and with >5% Incidence in THYMOGLOBULIN Patients
Adverse Reaction | THYMOGLOBULIN (N=82) | Active Comparator [ATG-E] (N=81)
Chills | 45 (55%) | 28 (35%)
Leukopenia | 40 (49%) | 10 (12%)
Fever | 38 (46%) | 39 (48%)
Nausea | 24 (29%) | 17 (21%)
Thrombocytopenia | 24 (29%) | 30 (37%)
Headache | 22 (27%) | 22 (27%)
Hypertension | 22 (27%) | 16 (20%)
Pain | 21 (26%) | 19 (24%)
Tachycardia | 19 (23%) | 16 (20%)
Diarrhea | 16 (20%) | 15 (19%)
Peripheral edema | 16 (20%) | 13 (16%)
Vomiting | 16 (20%) | 12 (15%)
Abdominal pain | 14 (17%) | 13 (16%)
Hyperkalemia | 14 (17%) | 12 (15%)
Arthralgia | 12 (15%) | 11 (14%)
Constipation | 12 (15%) | 16 (20%)
Dyspnea | 12 (15%) | 11 (14%)
Asthenia | 11 (13%) | 11 (14%)
Leukocytosis | 11 (13%) | 9 (11%)
Anemia | 10 (12%) | 11 (14%)
Back pain | 10 (12%) | 8 (10%)
Hypokalemia | 10 (12%) | 7 (9%)
Insomnia | 10 (12%) | 4 (5%)
Lung disorder | 10 (12%) | 6 (7%)
Myalgia | 9 (11%) | 7 (9%)
Dyspepsia | 8 (10%) | 6 (7%)
Hypotension | 8 (10%) | 2 (3%)
Acidosis | 7 (9%) | 4 (5%)
Chest pain | 7 (9%) | 7 (9%)
Malaise | 7 (9%) | 3 (4%)
Anxiety | 6 (7%) | 8 (10%)
Anorexia | 5 (6%) | 1 (1%)
Cough increased | 6 (7%) | 8 (10%)
Rash | 6 (7%) | 4 (5%)
Edema | 5 (6%) | 12 (15%)
Hypophosphatemia | 5 (6%) | 3 (4%)
Itchiness | 5 (6%) | 4 (5%)
Sweating | 5 (6%) | 4 (5%)
* Treatment-emergent adverse events that occurred during or within 24 hours of an infusion are summarized.

Treatment-emergent serum sickness was reported in 2 (2%) of patients following THYMOGLOBULIN infusion and in no patients following Active Comparator infusion.

6.2 Postmarketing Experience

The following adverse reactions have been identified during postapproval use of THYMOGLOBULIN. Because these adverse reactions are reported voluntarily from a population of uncertain size, it is not always possible to reliably estimate their frequency or establish a causal relationship to drug exposure.

- Hepatobiliary disorders: Hepatic dysfunction including transient reversible elevations in aminotransferases without any clinical signs or symptoms, hepatic failure, hyperbilirubinemia.
- Blood and lymphatic system disorders: Febrile neutropenia, coagulopathy without clinical signs or symptoms of bleeding, disseminated intravascular coagulopathy, anemia including hemolytic anemia, thrombotic microangiopathy.
- Immune system disorders: Hypersensitivity reactions including anaphylaxis, CRS.

7 DRUG INTERACTIONS

No drug interaction studies have been performed.

THYMOGLOBULIN can stimulate the production of antibodies that cross-react with rabbit immune globulins [see Clinical Pharmacology (12.3)].

8 USE IN SPECIFIC POPULATIONS

8.1 Pregnancy

Risk Summary

Animal reproduction studies have not been conducted with THYMOGLOBULIN. It is also not known whether THYMOGLOBULIN can cause fetal harm. THYMOGLOBULIN should be given to a pregnant woman only if the benefit outweighs the risk.

8.2 Lactation

Risk Summary

THYMOGLOBULIN has not been studied in nursing women. It is not known whether this drug is excreted in human milk. Because other immunoglobulins are excreted in human milk, breastfeeding should be discontinued during THYMOGLOBULIN therapy.

8.3 Females and Males of Reproductive Potential

Contraception

Females

There is a lack of information on the risks associated with the administration of THYMOGLOBULIN during pregnancy. Therefore, effective contraception is recommended during and for a minimum of 3 months after treatment.

8.4 Pediatric Use

The safety and effectiveness of THYMOGLOBULIN in pediatric patients have been established in pediatric patients for the prophylaxis and treatment of acute rejection. The use of THYMOGLOBULIN in pediatric patients was supported by extrapolation of adult data from Study 1, Study 2 and Study 3 [see Adverse Reactions (6) and Clinical Studies (14)].

10 OVERDOSAGE

THYMOGLOBULIN overdosage may result in leukopenia (including lymphopenia and neutropenia) and/ or thrombocytopenia, which can be managed with dose reduction [see Dosage and Administration (2.1, 2.3)].

11 DESCRIPTION

THYMOGLOBULIN® (anti-thymocyte globulin [rabbit]) is a purified, pasteurized, immunoglobulin G, obtained by immunization of rabbits with human thymocytes. This immunosuppressive product contains cytotoxic antibodies directed against antigens expressed on human T-lymphocytes.

THYMOGLOBULIN is a sterile, lyophilized powder for intravenous administration after reconstitution with sterile Water for Injection, USP (SWFI). Each single-dose 10 mL vial contains 25 mg of anti-thymocyte globulin (rabbit), 50 mg glycine, 10 mg sodium chloride, and 50 mg mannitol.

After reconstitution with 5 mL SWFI, each vial of reconstituted product contains approximately 5 mg/mL of THYMOGLOBULIN, of which >90% is rabbit gamma immune globulin (IgG). The reconstituted solution has a pH of 6.5 to 7.2.

Human red blood cells are used in the manufacturing process to deplete cross-reactive antibodies to non–T-cell antigens. The manufacturing process is validated to remove or inactivate potential exogenous viruses. All human red blood cells are from U.S.-registered or FDA-licensed blood banks. A virus removal step (nanofiltration, using a 20 nm filter) and a viral inactivation step (pasteurization, i.e., heat treatment of active ingredient at 60°C/10 hr) are performed for each lot. Each THYMOGLOBULIN lot is released following potency testing (lymphocytotoxicity and anti-CD2 binding inhibition), and cross-reactive antibody testing (hemagglutination, platelet agglutination, and fibroblast toxicity assays on every lot).

12 CLINICAL PHARMACOLOGY

12.1 Mechanism of Action

The mechanism of action by which polyclonal antilymphocyte preparations suppress immune responses is not fully understood. Possible mechanisms by which THYMOGLOBULIN may induce immunosuppression in vivo include: T-cell clearance from the circulation and modulation of T-cell activation, homing, and cytotoxic activities. THYMOGLOBULIN includes antibodies against T-cell markers such as CD2, CD3, CD4, CD8, CD11a, CD18, CD25, CD44, CD45, HLA-DR, HLA Class I heavy chains, and ß2 micro-globulin. In vitro, THYMOGLOBULIN (concentrations >0.1 mg/mL) mediates T-cell suppressive effects via inhibition of proliferative responses to several mitogens. In patients, T-cell depletion is usually observed within a day after initiating THYMOGLOBULIN therapy.

THYMOGLOBULIN has not been shown to be effective for treating antibody-mediated (humoral) rejections.

12.3 Pharmacokinetics

After an intravenous dose of 1.25 to 1.5 mg/kg/day (over 4 hours for 7–11 days) 4–8 hours post infusion, THYMOGLOBULIN levels were on average 21.5 mcg/mL (10–40 mcg/mL) with a half-life of 2–3 days after the first dose, and 87 mcg/mL (23–170 mcg/mL) after the last dose.

During the THYMOGLOBULIN Phase 3 randomized trial for the treatment of acute rejection, of the 108 of 163 patients evaluated, anti-rabbit antibodies developed in 68% of the THYMOGLOBULIN-treated patients, and anti-horse antibodies developed in 78% of the Active Comparator-treated patients. No controlled studies have been conducted to study the effect of anti-rabbit antibodies on repeat use of THYMOGLOBULIN. However, to ensure that T-cell depletion is achieved upon retreatment with THYMOGLOBULIN, monitoring the lymphocyte count is recommended. T-cell counts based on data collected from a limited number of patients (n=12) in this study, are presented in the chart below. These data were collected using flow cytometry (FACSCAN, Becton-Dickinson).

14 CLINICAL STUDIES

14.1 Prophylaxis of Acute Rejection in Patients Receiving a Kidney Transplant

Study 1 (NCT00235300)

THYMOGLOBULIN was evaluated in an open-label, randomized, active-controlled study in kidney transplant patients (n=278) at increased risk of acute rejection or delayed graft function.

The treatment failure rate within 12 months post-transplantation was statistically significantly lower in the THYMOGLOBULIN group than in the Active Comparator group (25% vs 38%; p=0.02), based on the composite endpoint (biopsy-proven acute rejection [BPAR], graft loss [GL], or death, with "lost to follow-up" considered as a treatment failure). The individual elements of the composite endpoint were BPAR (13% vs 21%), GL (8% vs 10%), and death (4% vs 4%) for the THYMOGLOBULIN and Active Comparator groups, respectively (Table 7).

Table 7: Prophylaxis of Acute Rejection – Treatment Failure within 12 Months (Study 1)
Parameter | THYMOGLOBULIN (N=141) | Active Comparator [basiliximab] (N=137) | Difference [Two-sided 95% confidence intervals of difference between treatment groups (THYMOGLOBULIN – Active Comparator) are based on normal approximation of binomial distribution.] (95% CI) | P-value [P-value obtained by comparison of treatment groups using Fisher's exact test.]
Composite endpoint | 35/141 (25%) | 52/137 (38%) | -13% (-23.9% to -2.3%) | 0.02
BPAR | 18/141 (13%) | 29/137 (21%) | -8% (-17.2% to 0.4%) | –
Graft loss | 11/141 (8%) | 13/137 (10%) | – | –
Death | 6/141 (4%) | 6/137 (4%) | – | –
Lost to follow-up [Lost to follow-up is defined as not having BPAR, GL, or death within 12 months after transplantation, and last visit date was prior to the lower bound of 12-month window (12 months ± 30 days after transplantation).] | 7/141 (5%) | 11/137 (8%) | – | –
BPAR= biopsy-proven acute rejection; CI=confidence interval

The composite endpoint is defined as the occurrence of any of the following: BPAR (Grade I–III), graft loss, death, or lost to follow-up. Except for patients counted as "lost to follow-up," a patient can be counted in more than one category for the individual components (BPAR, graft loss, death).

In Study 1, patients received either THYMOGLOBULIN (n=141) 1.5 mg/kg daily for a total of 5 doses (Day 0 to Day 4) or Active Comparator (n=137) 2 doses of 20 mg each (Day 0, Day 4). For both treatment groups, the first induction treatment was initiated prior to the reperfusion of the kidney. All patients received triple maintenance immunosuppression (cyclosporine, mycophenolate mofetil, and corticosteroids) throughout the 12 months of the study.

Recipient disease characteristics were balanced between the 2 treatment groups with similar distribution of prior transplant, degree of sensitization and number of mismatched human leukocyte antigens (HLA). Overall, the mean percentage of pretransplant panel-reactive antibody (PRA) was 6% and the historical peak was 14%. The number of patients having a higher level of sensitization with PRA >20% was similar in the THYMOGLOBULIN (9%) and Active Comparator (10%) groups. The mean number of mismatched HLAs was evenly distributed across the 2 treatment groups.

Study 2 (NCT00682292)

THYMOGLOBULIN was evaluated in an open-label, parallel-arm, randomized, active-controlled, investigator-sponsored study in kidney transplant patients (n=230) at higher immunological risk of rejection.

The noninferiority of THYMOGLOBULIN to Active Comparator was achieved with treatment failure rates of 25% versus 34%, with an estimated treatment group difference (THYMOGLOBULIN – Active Comparator) of -9% (95% CI: -19.9% to 3.6%), based on the composite endpoint (BPAR, GL, or death, with lost to follow-up considered as a treatment failure) in the 12 months after transplantation. The individual elements of the composite endpoint were BPAR (11% vs 21%), GL (15% vs 11%), and death (4% vs 3%) for the THYMOGLOBULIN and Active Comparator groups, respectively (Table 8).

Table 8: Prophylaxis of Acute Rejection – Treatment Failure within 12 Months (Study 2)
Parameter | THYMOGLOBULIN (N=114) | Active Comparator [daclizumab] (N=116) | Difference [Two-sided 95% confidence intervals of difference between treatment groups (THYMOGLOBULIN – Active Comparator) are based on normal approximation of binomial distribution.] (95% CI)
Composite endpoint | 29 (25%) | 39 (34%) | -9% (-19.9% to 3.6%)
BPAR | 12 (11%) | 24 (21%) | -10% (-19.4% to -0.9%)
Graft loss | 17 (15%) | 13 (11%) | –
Death | 5 (4%) | 4 (3%) | –
Lost to follow-up [Lost to follow-up is defined as not having BPAR (Grade I–III), GL, or death within 12 months post-transplantation, and last visit date was prior to the lower bound of 12 month window (12 months ± 30 days post-transplantation).] | 2 (2%) | 3 (3%) | –
BPAR= biopsy-proven acute rejection; CI=confidence interval
The composite endpoint is defined as the occurrence of any of the following: BPAR (Grade I–III), graft loss, death, or lost to follow-up. A patient can be counted in more than one category with the exception of lost to follow-up.

In Study 2, patients received either THYMOGLOBULIN (n=114) 1.25 mg/kg daily for a total of 8 doses (Day 0 to Day 7) or Active Comparator (n=116) 1 mg/kg (maximum dose 100 mg) on Days 0, 14, 28, 42, and 56. For both treatment groups, the first induction treatment was initiated prior to the beginning of the surgical procedure. All patients received triple maintenance immunosuppression (tacrolimus, mycophenolate mofetil, and corticosteroids) throughout the 12 months of the study.

Recipient disease characteristics were balanced between the 2 treatment groups, including similar distribution of prior transplant, degree of sensitization and number of HLA mismatches. The number of patients having prior transplants was 163 of 230 (71%). Overall, the mean percentage of pretransplant PRA was 35% and the historical peak was 72%. The number of patients having a higher level of sensitization with PRA >20% was similar in the THYMOGLOBULIN (55%) and Active Comparator (58%) groups. The mean number of HLA mismatches was evenly distributed across the 2 treatment groups.

14.2 Treatment of Acute Rejection in Patients Receiving a Kidney Transplant

Study 3

A controlled, double-blind, multicenter, randomized clinical trial comparing THYMOGLOBULIN and Active Comparator was conducted at 28 US transplant centers in renal transplant patients (n=163) with biopsy-proven Banff Grade II (moderate), Grade III (severe), or steroid-resistant Grade I (mild) acute graft rejection. This clinical trial met the non-inferiority criteria for THYMOGLOBULIN relative to Active Comparator in reversing acute rejection episodes with a 20% non-inferiority margin. The overall weighted estimate of the treatment difference (THYMOGLOBULIN – Active Comparator success rate) was 11% with a lower 95% confidence bound of 0.07%. Therefore, THYMOGLOBULIN was not inferior to Active Comparator in reversing acute rejection episodes.

In the study, patients were randomized to receive 7 to 14 days of THYMOGLOBULIN (1.5 mg/kg/day) or Active Comparator (15 mg/kg/day). For the entire study, the two treatment groups were comparable with respect to donor and recipient characteristics. In Table 9, successful treatment is presented as those patients whose serum creatinine levels (14 days from the diagnosis of rejection) returned to baseline and whose graft was functioning on Day 30 after the end of therapy.

Table 9: Treatment of Acute Rejection – Response to Study Treatment by Rejection Severity
Success/n | Total
 | Thymoglobulin | Active Comparator [ATG-E]
Rejection Severity:
Mild | 9/10 (90%) | 5/8 (63%)
Moderate | 44/58 (76%) | 41/58 (71%)
Severe | 11/14 (72%) | 8/14 (57%)
Overall | 64/82 (78%) | 54/80 (68%)
Weighted estimate of difference (Thymoglobulin – Active Comparator) |  | 11%
Lower one-sided 95% confidence bound |  | 0.07%
p Value [under null hypothesis (Cochran-Mantel-Haenszel test)] |  | 0.061

There were no statistically significant differences between the two treatments with respect to (1) serum creatinine levels 30 days after treatment relative to baseline, (2) improvement rate in post-treatment histology, (3) one-year post-rejection Kaplan-Meier patient survival (THYMOGLOBULIN 93%, n=82 and Active Comparator 96%, n=80), (4) Day 30 post-rejection graft survival and (5) one-year post-rejection graft survival (THYMOGLOBULIN 83%, n=82; Active Comparator 75%, n=80).

16 HOW SUPPLIED/STORAGE AND HANDLING

16.1 How Supplied

THYMOGLOBULIN is supplied as a single-dose clear glass 10 mL vial containing 25 mg of lyophilized (solid) THYMOGLOBULIN. Each carton contains one THYMOGLOBULIN vial (NDC 58468-0080-1).

16.2 Storage and Handling

- Store in refrigerator at 2°C to 8°C (36°F to 46°F).
- Protect from light.
- Do not freeze.
- Do not use after the expiration date indicated on the label.
- Reconstituted THYMOGLOBULIN is physically and chemically stable for up to 24 hours at room temperature; however, room temperature storage is not recommended. As THYMOGLOBULIN contains no preservatives, reconstituted product should be used immediately.
- Infusion solutions of THYMOGLOBULIN must be used immediately.
- Any unused drug remaining after infusion must be discarded.

17 PATIENT COUNSELING INFORMATION

Advise patients receiving THYMOGLOBULIN that they will be monitored by a physician experienced in immunosuppressive therapy for the management of kidney transplant patients [see Warnings and Precautions (5.1)].

Hypersensitivity and Infusion-Related Reactions

Advise patients of the signs and symptoms of infusion-related reactions (flu-like symptoms, e.g., fever, chills, nausea, muscle or joint pain) and the need to take premedications as prescribed.

Determine if the patient has known allergies to rabbits or rabbit proteins. Determine if the patient has had significant exposure to rabbits [see Warnings and Precautions (5.2) and Adverse Reactions (6.2)].

Infections

Inform patients of the increased risk of infection while taking immunosuppressive therapy. Instruct patients to immediately report signs or symptoms of infection and to take prophylactic anti-infectives as prescribed [see Warnings and Precautions (5.4) and Adverse Reactions (6.2)].

Malignancies

Inform patients of the increased risk of malignancies, especially skin cancer, while taking immunosuppressive therapy. Instruct patients to limit exposure to sunlight and UV light by wearing protective clothing and using sunscreen with a high protection factor [see Warnings and Precautions (5.5) and Adverse Reactions (6.2)].

Immunizations

Advise patients that they should not receive immunizations with live viral vaccines if they have been recently treated with THYMOGLOBULIN [see Warnings and Precautions (5.6)].

Manufactured for:
Genzyme Corporation
Cambridge, MA 02141
A SANOFI COMPANY
U.S. License No. 1596

By:
Sanofi Winthrop Industrie
Lyon, France

©2026 Genzyme Corporation. All rights reserved.

PRINCIPAL DISPLAY PANEL - 25 mg Vial Carton

NDC 58468-0080-1
Rx only

Thymoglobulin®
Anti-thymocyte Globulin (Rabbit)

25 mg per vial

For Injection
For Intravenous Infusion

One single-dose vial
Discard unused portion

SANOFI GENZYME